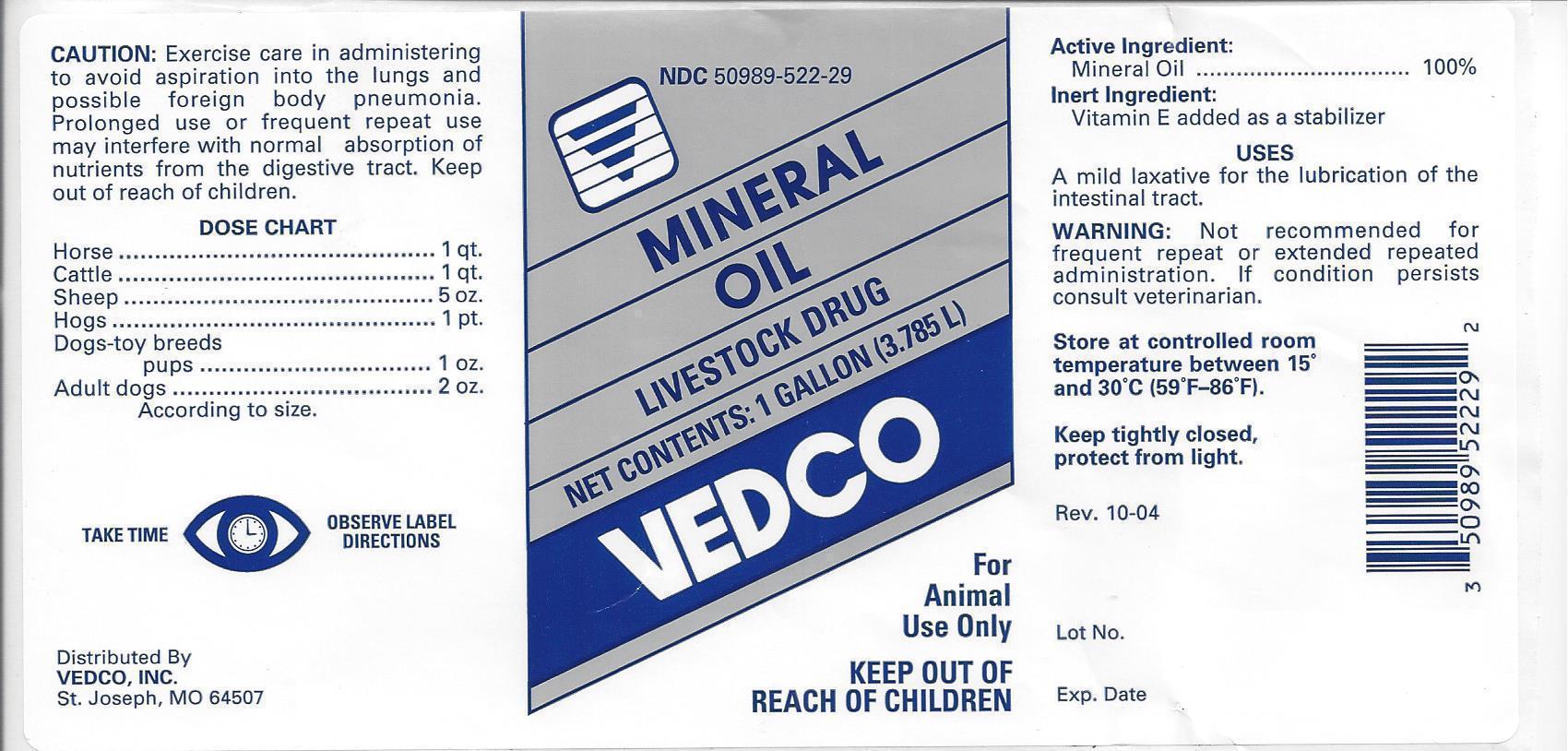 DRUG LABEL: MINERAL OIL LIGHT
NDC: 50989-522 | Form: LIQUID
Manufacturer: VEDCO
Category: animal | Type: OTC ANIMAL DRUG LABEL
Date: 20130830

ACTIVE INGREDIENTS: LIGHT MINERAL OIL 3.45 kg/3.45 kg

VEDCO MINERAL OIL

NDC 50989-522-29 MINERAL OIL LIVESTOCK DRUG NET CONTENTS: 1 GALLON (3.785L) VEDCO

For Animal Use Only

KEEP OUT OF REACH OF CHILDREN

CAUTION:

Excercise care in administering to avoid aspiration into the lungs and possible foreign body pneumonia. Prolonged use or frequent repeat use may interfere with normal absorption of nutrients from the digestive tract. Keep out of reach of childern.

Dose Chart

Horse………………………………….………1 qt.

Cattle…………………………………………1 qt.

Sheep…………………………………………5 oz.

Hogs…………………………………………..1 pt.

Dogs-toy breeds

pups……………................1 oz.

Adult dogs....……………………………..2 oz.

According to size.

WARNINGS

TAKE TIME

OBSERVE LABEL DIRECTIONS

INFORMATION FOR OWNERS/CAREGIVERS

Distributed By

VEDCO, INC.

St. Joseph, MO 64507

Active Ingredient:

Mineral oil……………………………………….100%

Inert Ingredient:

Vitamin E added as a stabilizer

USES

A mild laxative for the lubrication of the intestinal tract.

WARNING:

Not recommended for frequent repeat or extended repeated administration. If condition persists consult veterinarian.

STORAGE AND HANDLING

Store at controlled room temperature between 15^0 and 30^0 C (59^0F-86^0F)

Keep tightly closed, protect from light.